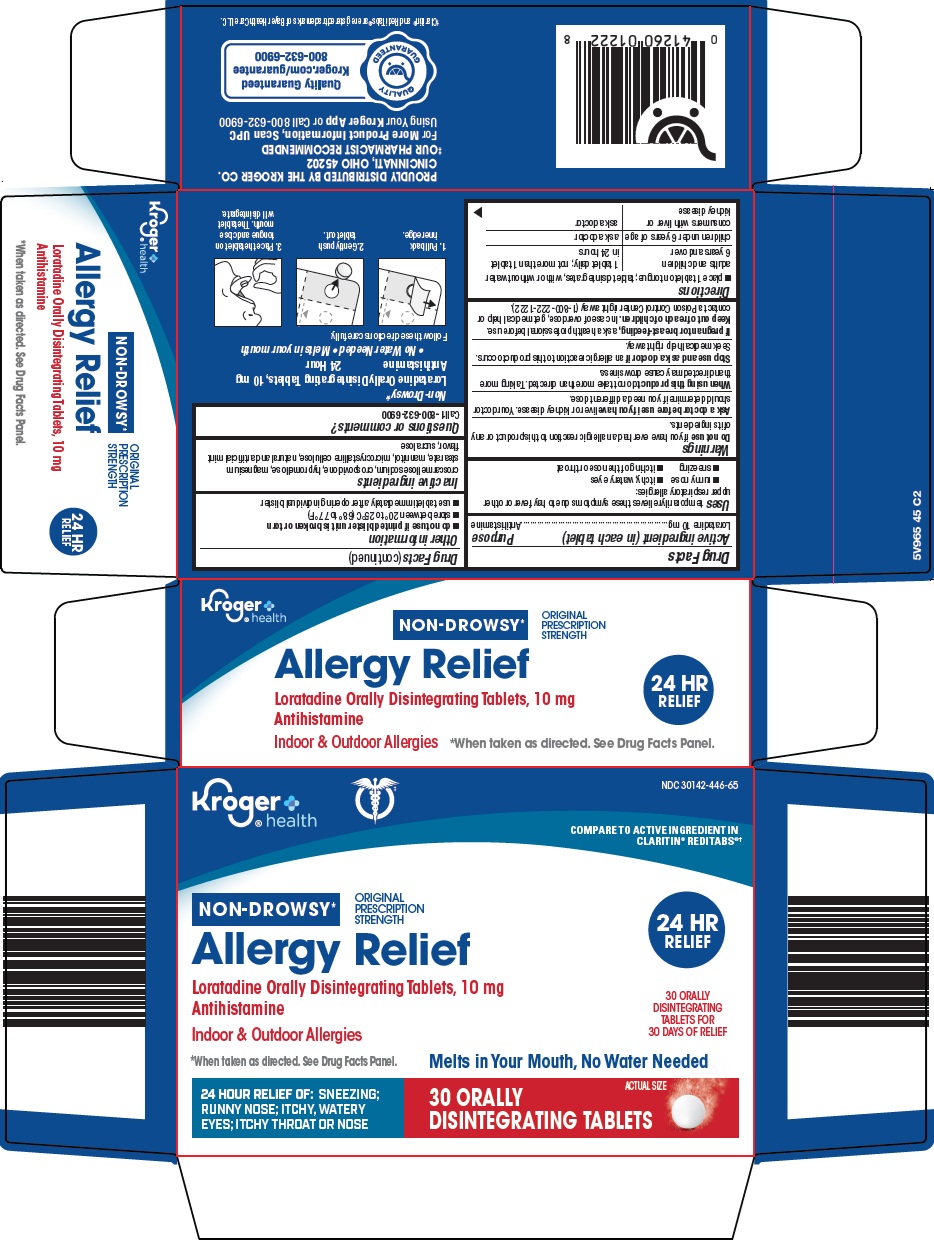 DRUG LABEL: allergy relief
NDC: 30142-446 | Form: TABLET, ORALLY DISINTEGRATING
Manufacturer: Kroger Company
Category: otc | Type: HUMAN OTC DRUG LABEL
Date: 20260224

ACTIVE INGREDIENTS: LORATADINE 10 mg/1 1
INACTIVE INGREDIENTS: CROSCARMELLOSE SODIUM; CROSPOVIDONE (120 .MU.M); HYPROMELLOSE, UNSPECIFIED; MAGNESIUM STEARATE; MANNITOL; MICROCRYSTALLINE CELLULOSE; SUCRALOSE

Kroger Co. Allergy Relief Drug Facts

Active ingredient (in each tablet)

Loratadine 10 mg

Purpose

Antihistamine

Uses

temporarily relieves these symptoms due to hay fever or other upper respiratory allergies:

- runny nose
- itchy, watery eyes
- sneezing
- itching of the nose or throat

Warnings

Do not use

if you have ever had an allergic reaction to this product or any of its ingredients.

Ask a doctor before use if you have

liver or kidney disease. Your doctor should determine if you need a different dose.

When using this product

do not take more than directed. Taking more than directed may cause drowsiness.

Stop use and ask a doctor if

an allergic reaction to this product occurs. Seek medical help right away.

If pregnant or breast-feeding,

ask a health professional before use.

Keep out of reach of children.

In case of overdose, get medical help or contact a Poison Control Center right away (1-800-222-1222).

Directions

- place 1 tablet on tongue; tablet disintegrates, with or without water

adults and children 6 years and over | 1 tablet daily; not more than 1 tablet in 24 hours
children under 6 years of age | ask a doctor
consumers with liver or kidney disease | ask a doctor

Other information

- do not use if printed blister unit is broken or torn
- store between 20° to 25°C (68° to 77°F)
- use tablet immediately after opening individual blister

Inactive ingredients

croscarmellose sodium, crospovidone, hypromellose, magnesium stearate, mannitol, microcrystalline cellulose, natural and artificial mint flavor, sucralose

Questions or comments?

Call 1-800-632-6900

Package/Label Principal Display Panel

Kroger® health

COMPARE TO ACTIVE INGREDIENT IN CLARITIN® REDITABS®

NON-DROWSY*

ORIGINAL PRESCRIPTION STRENGTH

24 HR RELIEF

Allergy Relief

Loratadine Orally Disintegrating Tablets, 10 mg

Antihistamine

30 ORALLY DISINTEGRATING TABLETS FOR 30 DAYS OF RELIEF

Indoor & Outdoor Allergies

*When taken as directed. See Drug Facts Panel.

Melts in Your Mouth, No Water Needed

24 HOUR RELIEF OF: SNEEZING; RUNNY NOSE; ITCHY, WATERY EYES; ITCHY THROAT OR NOSE

30 ORALLY DISINTEGRATING TABLETS

ACTUAL SIZE